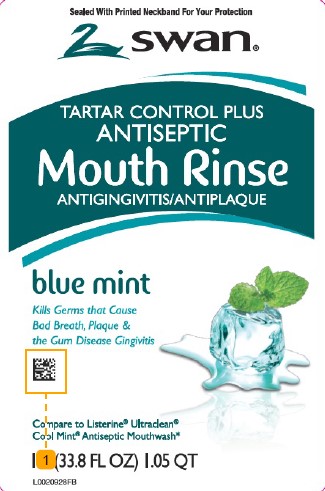 DRUG LABEL: Tartar control plus Antiseptic
NDC: 11344-855 | Form: MOUTHWASH
Manufacturer: Consumer Product Partners, LLC
Category: otc | Type: HUMAN OTC DRUG LABEL
Date: 20250211

ACTIVE INGREDIENTS: EUCALYPTOL 0.92 mg/1 mL; MENTHOL 0.42 mg/1 mL; METHYL SALICYLATE 0.6 mg/1 mL; THYMOL 0.64 mg/1 mL
INACTIVE INGREDIENTS: WATER; ALCOHOL; SORBITOL; POLOXAMER 407; BENZOIC ACID; ZINC CHLORIDE; SODIUM BENZOATE; SUCRALOSE; SACCHARIN SODIUM; FD&C GREEN NO. 3

Swan 855.000/855AC
Tartar Control Plus Antiseptic Mouth Rinse, Blue Mint

Claims

TARTAR CONTROL PLUS

ANTISEPTIC

Mouth Rinse

ANTIGINGIVITS/ANTIPLAQUE

Active ingredients

Eucalyptol 0.092%

Menthol 0.042%

Methyl salicylate 0.060%

Thymol 0.064%

Purpose

Antigingivitis, Antiplaque

Use

helps control plaque that leads to gingivitis

Warnings

for this product

Do not use

if you have painful or swollen gums, pus from the gum line, loose teeth or increased spacing between the teeth. See your dentist immediately. These may be signs of periodontitis, a serious form of gum disease.

Stop use and ask a dentist if

gingivitis, bleeding, or redness persists for more than 2 weeks

Keep out of reach of children.

If more than used for rinsing is accidentally swallowed, get medical help or contact a Poison Control Center right away.

Directions

adults and children 12 years of age and older - vigorously swish 20 mL (2/3 FL OZ or 4 teaspoonfuls) between teeth twice a day for 30 seconds then spit out; do not swallow

children 6 years to under 12 years of age - supervise use

children under 6 years of age - do not use

- this rinse is not intended to replace brushing or flossing

Other information

cold weather may cloud this product. Its antiseptic properties are not affected. Store at room temperature (59°to 86°F)

Inactive ingredients

water, alcohol (21.6%), sorbitol, flavor, poloxamer 407, benzoic acid, zinc chloride, sodium benzoate, sucralose, sodium saccharin, green 3

Disclaimer

*This product is not manufactured or distributed by Kenvue, Inc., distributer of Listerine®Ultraclean®Cool Mint® Antiseptic Mouthwash.

Adverse reaction

Distributed by:

Consumer Product Partners, LLC,

St. Louis, MO 63114

1-888-593-0593

DSP-TN-21091

DSP-MO-20087

Principal Panel Display

Sealed With Printed Neckband For Your Protection

swan ®

TARTAR CONTROL PLUS

ANTISEPTIC

Mouth Rinse

ANTIGINGIVITIS/ANTIPLAQUE

blue mint

Kills Germs that Cause Bad Breath, Plaque & the Gum Disease Gingivitis

Compare to Listerine®Ultraclean® Cool Mint® Antiseptic Mouthwash*

1 LITER (33.8 FL OZ) 1.05 QT